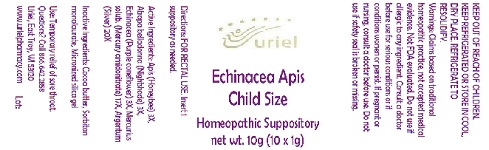 DRUG LABEL: Echinacea Apis Child Size
NDC: 48951-4012 | Form: SUPPOSITORY
Manufacturer: Uriel Pharmacy Inc.
Category: homeopathic | Type: HUMAN OTC DRUG LABEL
Date: 20210615

ACTIVE INGREDIENTS: APIS MELLIFERA 3 [hp_X]/1 g; ATROPA BELLADONNA 3 [hp_X]/1 g; ECHINACEA ANGUSTIFOLIA 3 [hp_X]/1 g; MERCURIUS SOLUBILIS 17 [hp_X]/1 g; SILVER 20 [hp_X]/1 g
INACTIVE INGREDIENTS: COCOA BUTTER; CORN OIL; SILICON DIOXIDE

Echinacea Apis Child Size

INDICATIONS AND USAGE

Directions: FOR RECTAL USE.

DOSAGE AND ADMINISTRATION

Insert 1 suppository as needed.

ACTIVE INGREDIENT

Active Ingredients: Apis (Honeybee) 3X, Atropa belladonna (Nightshade) 3X, Echinacea (Purple coneflower) 3X, Mercurius solub. (Mercury amidonitrate) 17X, Argentum (Silver) 20X

INACTIVE INGREDIENT

Inactive Ingredients: Cocoa butter, Hydrogenated vegetable oil, Micronized silica gel

PURPOSE

Use: Temporary relief of sore throat.

KEEP OUT OF REACH OF CHILDREN

WARNINGS

KEEP REFRIGERATED OR STORE IN COOL, DRY PLACE. REFRIGERATE TO RESOLIDIFY.
Warnings: Claims based on traditional homeopathic practice, not accepted medical evidence. Not FDA evaluated. Do not use if allergic to any ingredient. Consult a doctor before use for serious conditions or if conditions worsen or persist. If pregnant or nursing, consult a doctor before use. Do not use if safety seal is broken or missing.

QUESTIONS

Questions? Call 866.642.2858 Uriel, East Troy, WI 53120 www.urielpharmacy.com